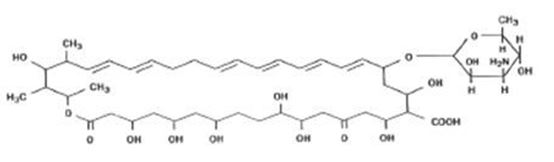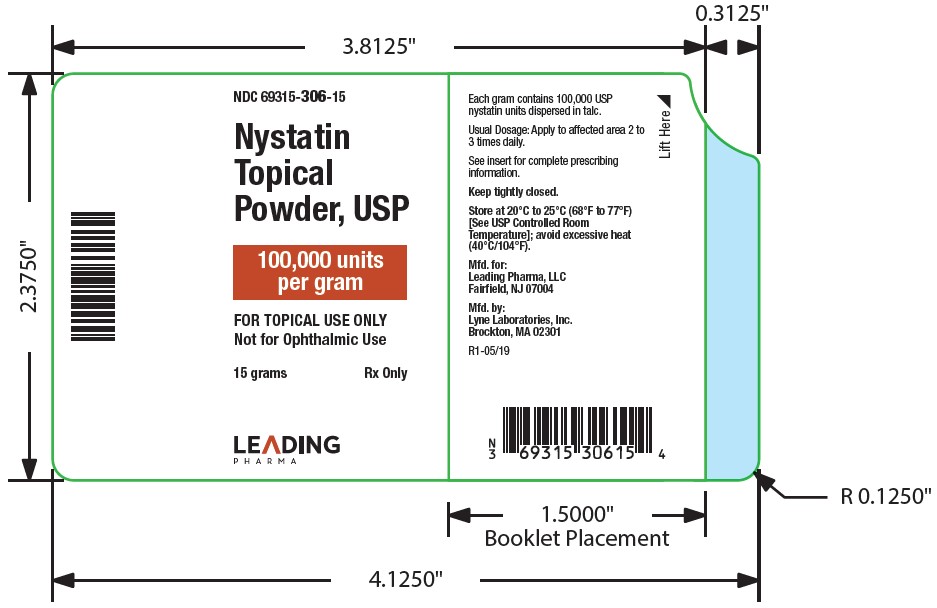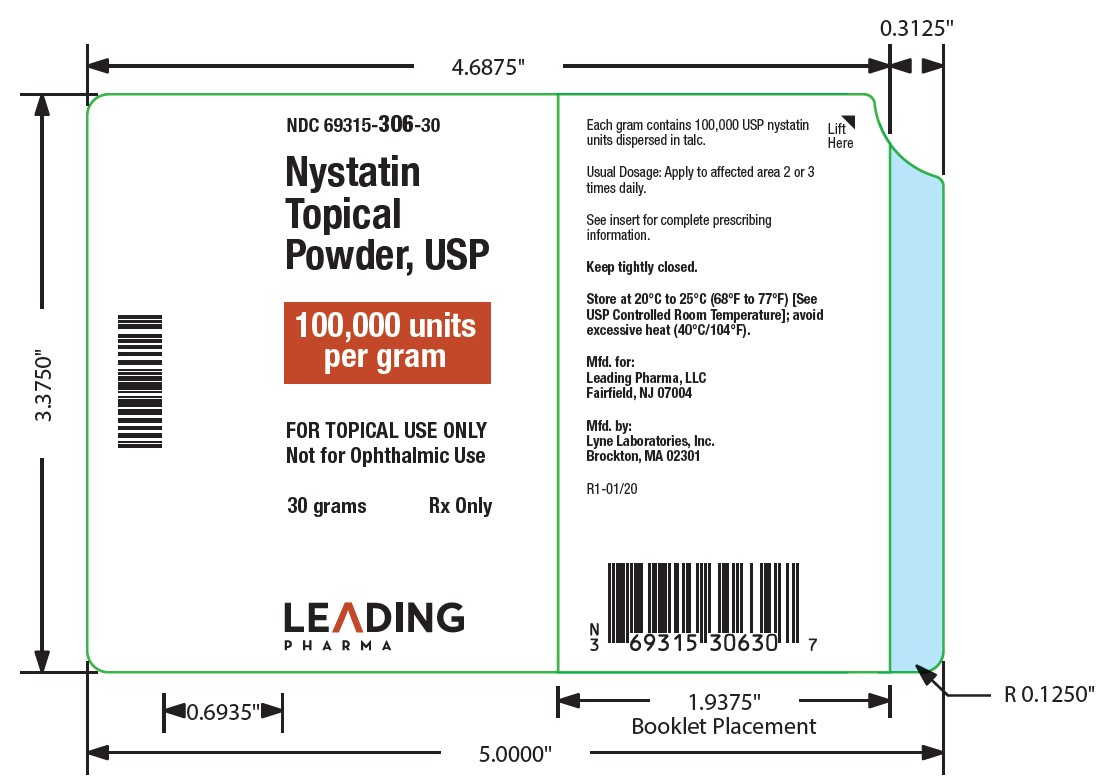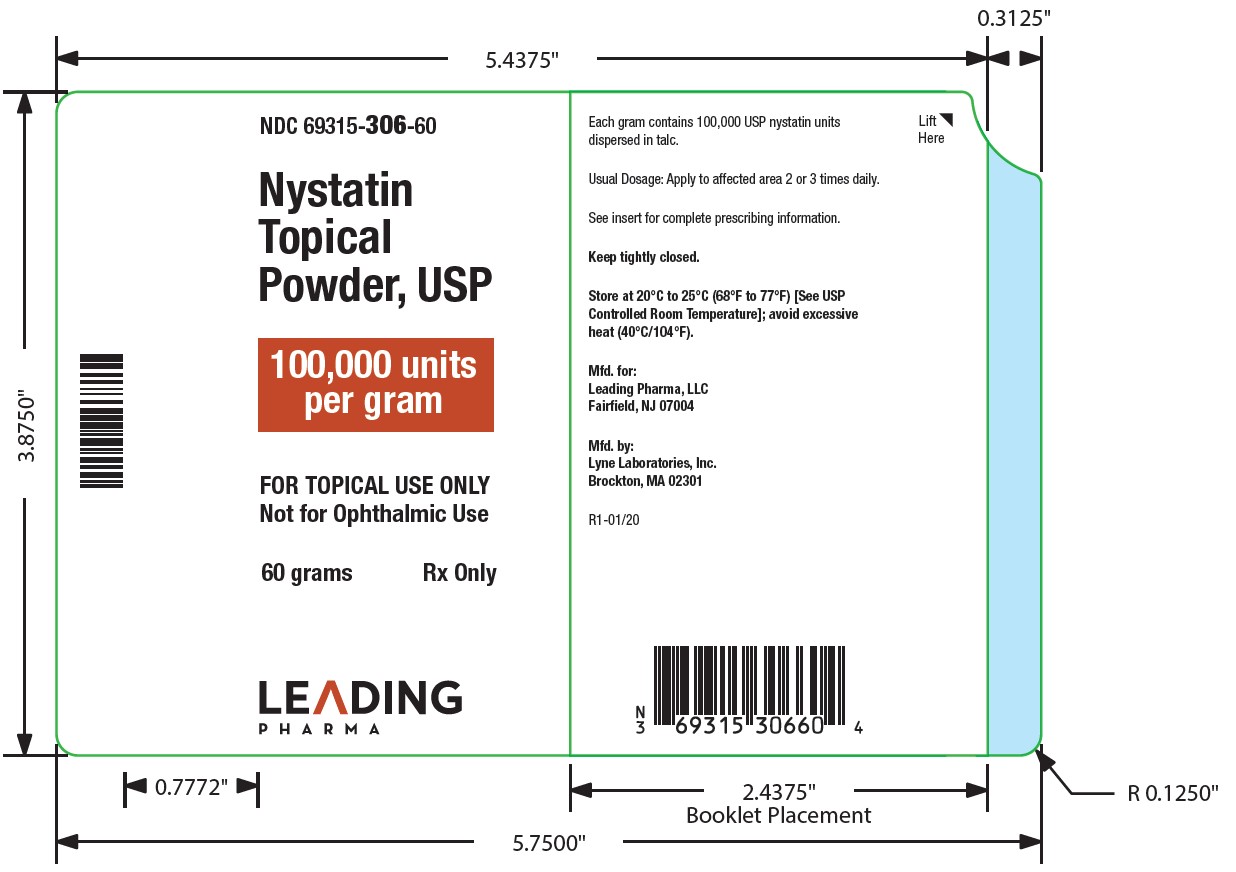 DRUG LABEL: NYSTATIN
NDC: 67296-1501 | Form: POWDER
Manufacturer: RedPharm Drug
Category: prescription | Type: HUMAN PRESCRIPTION DRUG LABEL
Date: 20240808

ACTIVE INGREDIENTS: NYSTATIN 100000 [USP'U]/1 g
INACTIVE INGREDIENTS: TALC

NYSTATIN TOPICAL POWDER
Rx Only
FOR TOPICAL USE ONLY.NOT FOR OPHTHALMIC USE

DESCRIPTION

Nystatin is a polyene antifungal antibiotic obtained from Streptomyces noursei. The molecular formula for Nystatin is C47H75NO17. The molecular weight of Nystatin is 926.1.
Structural formula:

Nystatin topical powder is for dermatologic use.
Nystatin topical powder contains 100,000 nystatin units per gram dispersed in talc.

CLINCAL PHARMACOLOGY

Pharmacokinetics

Nystatin is not absorbed from intact skin or mucous membrane.

Microbiology

Nystatin is an antibiotic which is both fungistatic and fungicidal in vitroagainst a wide variety of yeasts and yeast-like fungi, including Candida albicans, C. parapsilosis, C. tropicalis, C. guilliermondi, C. pseudotropicalis, C. krusei, Torulopsis glabrata, Tricophyton rubrum, T. mentagrophytes.

Nystatin acts by binding to sterols in the cell membrane of susceptible species resulting in a change in membrane permeability and the subsequent leakage of intracellular components. On repeated subculturing with increasing levels of nystatin, Candida albicans does not develop resistance to nystatin. Generally, resistance to nystatin does not develop during therapy. However, other species of Candida (C. tropicalis, C. guilliermondi, C. krusei, and C. stellatoides) become quite resistant on treatment with nystatin and simultaneously become cross resistant to amphotericin as well. This resistance is lost when the antibiotic is removed.

Nystatin exhibits no appreciable activity against bacteria, protozoa, or viruses.

INDICATIONS AND USAGE

Nystatin topical powder is indicated in the treatment of cutaneous or mucocutaneous mycotic infections caused by Candida albicansand other susceptible Candida species.

Nystatin topical powder is not indicated for systemic, oral, intravaginal or ophthalmic use.

CONTRAINDICATIONS

Nystatin topical powder is contraindicated in patients with a history of hypersensitivity to anyof its components.

PRECAUTIONS

General

Nystatin topical powder should not be used for the treatment of systemic, oral, intravaginal or ophthalmic infections.

If irritation or sensitization develops, treatment should be discontinued and appropriate measures taken as indicated. It is recommended that KOH smears, cultures, or other diagnostic methods be used to confirm the diagnosis of cutaneous or mucocutaneous candidiasis and to rule out infection caused by other pathogens

HOW SUPPLIED

Nystatin topical powder is supplied as 100,000 units nystatin per gram in plastic squeeze bottles:

15g (NDC 69315-306-15)

30g (NDC 69315-306-30)

60g (NDC 69315-306-60)

STORAGE

Store at 20°C to 25°C (68°F to 77°F)[see USP Controlled Room Temperature]; avoid excessive heat (40°C/104°F).

Keep tightly closed.

Manufactured for:

Leading Pharma LLC, Fairfield, NJ 07004

Manufactured by:

Lyne Laboratories, Inc. Brockton, MA 02301

R1-01/20